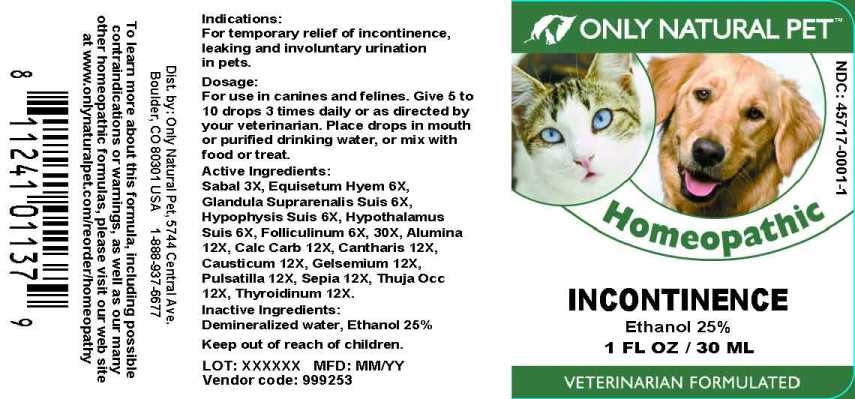 DRUG LABEL: Incontinence
NDC: 45717-0001 | Form: LIQUID
Manufacturer: Only Natural Pet Store
Category: homeopathic | Type: OTC ANIMAL DRUG LABEL
Date: 20241003

ACTIVE INGREDIENTS: SAW PALMETTO 3 [hp_X]/1 mL; EQUISETUM HYEMALE WHOLE 6 [hp_X]/1 mL; SUS SCROFA ADRENAL GLAND 6 [hp_X]/1 mL; SUS SCROFA PITUITARY GLAND 6 [hp_X]/1 mL; SUS SCROFA HYPOTHALAMUS 6 [hp_X]/1 mL; ESTRONE 6 [hp_X]/1 mL; ALUMINUM OXIDE 12 [hp_X]/1 mL; OYSTER SHELL CALCIUM CARBONATE, CRUDE 12 [hp_X]/1 mL; LYTTA VESICATORIA 12 [hp_X]/1 mL; CAUSTICUM 12 [hp_X]/1 mL; GELSEMIUM SEMPERVIRENS ROOT 12 [hp_X]/1 mL; PULSATILLA PRATENSIS WHOLE 12 [hp_X]/1 mL; SEPIA OFFICINALIS JUICE 12 [hp_X]/1 mL; THUJA OCCIDENTALIS LEAFY TWIG 12 [hp_X]/1 mL; THYROID 12 [hp_X]/1 mL
INACTIVE INGREDIENTS: WATER; ALCOHOL

Drug Facts:

ACTIVE INGREDIENTS:

Sabal Serrulata 3X, Equisetum Hyemale 6X, Glandula Suprarenalis Suis 6X, Hypophysis (Suis) 6X, Hypothalamus (Suis) 6X, Folliculinum 6X, 30X, Alumina 12X, Calcarea Carbonica 12X, Cantharis 12X, Causticum 12X, Gelsemium Sempervirens 12X, Pulsatilla (Pratensis) 12X, Sepia 12X, Thuja Occidentalis 12X, Thyroidinum (Suis) 12X.

INDICATIONS:

For temporary relief of incontinence, leaking and involuntary urination in pets.

WARNINGS:

To learn more about this formula, including possible contraindications or warnings, as well as our many other homeopathic formulas, please visit our web site at www.onlynaturalpet.com/reorder/homeopathy

KEEP OUT OF REACH OF CHILDREN:

DIRECTIONS:

For use in canines and felines. Give 5 to 10 drops 3 times daily or as directed by your veterinarian. Place drops in mouth or purified drinking water, or mix with food or treat.

INDICATIONS:

For temporary relief of incontinence, leaking and involuntary urination in pets.

INACTIVE INGREDIENTS:

Demineralized Water, Ethanol 25%

QUESTIONS:

Dist. by: Only Natural Pet, 5744 Central Ave.

Boulder, CO 80301 USA 1-888-937-6677

PRINCIPAL LABEL DISPLAY:

ONLY NATURAL PET

NDC: 45717-0001-1

Homeopathic

INCONTINENCE

1 FL OZ 30 ML

VETERINARIAN FORMULATED